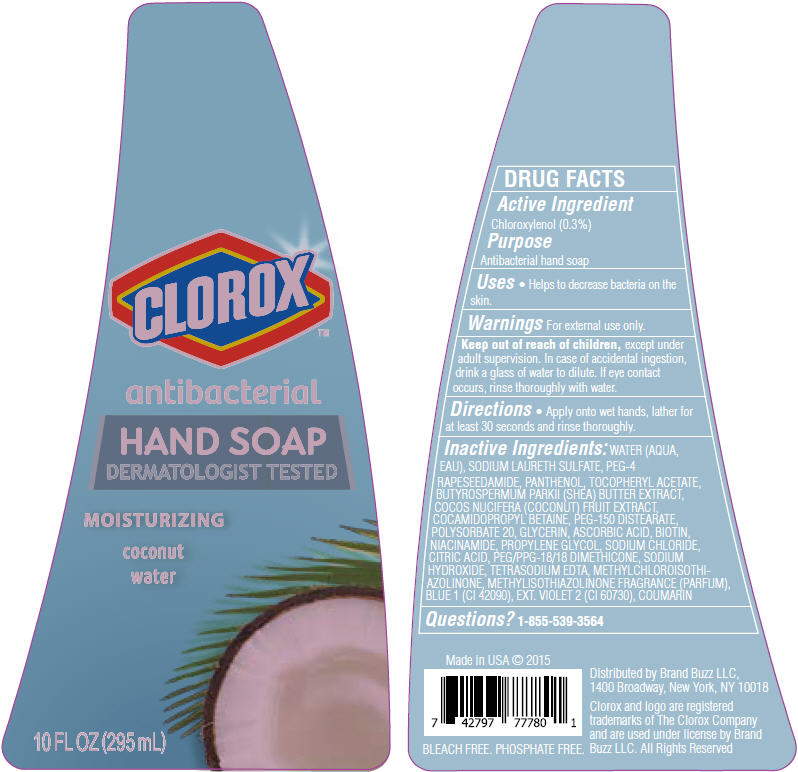 DRUG LABEL: Clorox Antibacterial Hand - Coconut Water
NDC: 69540-0074 | Form: SOAP
Manufacturer: Brand Buzz
Category: otc | Type: HUMAN OTC DRUG LABEL
Date: 20160106

ACTIVE INGREDIENTS: Chloroxylenol 0.003 g/1 mL
INACTIVE INGREDIENTS: Water; Sodium Laureth-3 Sulfate; PEG-4 Rapeseedamide; Panthenol; .Alpha.-Tocopherol Acetate; Sheanut oil; Coconut; Cocamidopropyl betaine; PEG-150 Distearate; Polysorbate 20; Glycerin; Ascorbic Acid; Biotin; Niacinamide; Propylene Glycol; Sodium Chloride; Citric Acid Monohydrate; PEG/PPG-18/18 Dimethicone; Sodium Hydroxide; Edetate Sodium; Methylchloroisothiazolinone; Methylisothiazolinone; FD&C Blue No. 1; Ext. D&C Violet No. 2; Coumarin

Clorox™ Antibacterial Hand Soap - Coconut Water

DRUG FACTS

Active Ingredient

Chloroxylenol (0.3%)

Purpose

Antibacterial hand soap

Uses

- Helps to decrease bacteria on the skin.

Warnings

For external use only.

Keep out of reach of children, except under adult supervision. In case of accidental ingestion, drink a glass of water to dilute. If eye contact occurs, rinse thoroughly with water.

Directions

- Apply onto wet hands, lather for at least 30 seconds and rinse thoroughly.

Inactive Ingredients

WATER (AQUA, EAU), SODIUM LAURETH SULFATE, PEG-4 RAPESEEDAMIDE, PANTHENOL, TOCOPHERYL ACETATE, BUTYROSPERMUM PARKII (SHEA) BUTTER EXTRACT, COCOS NUCIFERA (COCONUT) FRUIT EXTRACT, COCAMIDOPROPYL BETAINE, PEG-150 DISTEARATE, POLYSORBATE 20, GLYCERIN, ASCORBIC ACID, BIOTIN, NIACINAMIDE, PROPYLENE GLYCOL, SODIUM CHLORIDE, CITRIC ACID, PEG/PPG-18/18 DIMETHICONE, SODIUM HYDROXIDE, TETRASODIUM EDTA, METHYLCHLOROISOTHIAZOLINONE, METHYLISOTHIAZOLINONE FRAGRANCE (PARFUM), BLUE 1 (CI 42090), EXT. VIOLET 2 (CI 60730), COUMARIN

Questions?

1-855-539-3564

Distributed by Brand Buzz LLC,
1400 Broadway, New York, NY 10018

PRINCIPAL DISPLAY PANEL - 295 mL Bottle Label

CLOROX™

antibacterial

HAND SOAP
DERMATOLOGIST TESTED

MOISTURIZING

coconut
water

10 FL OZ (295 mL)